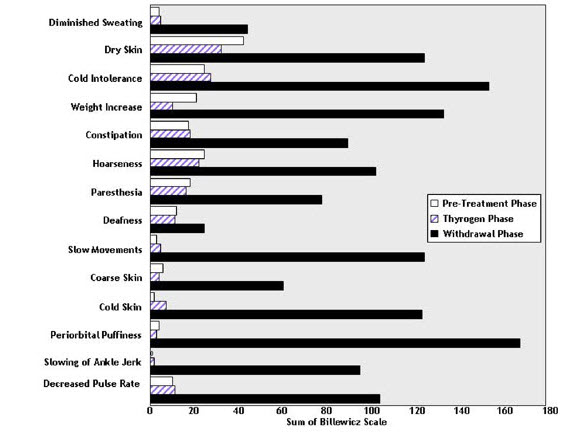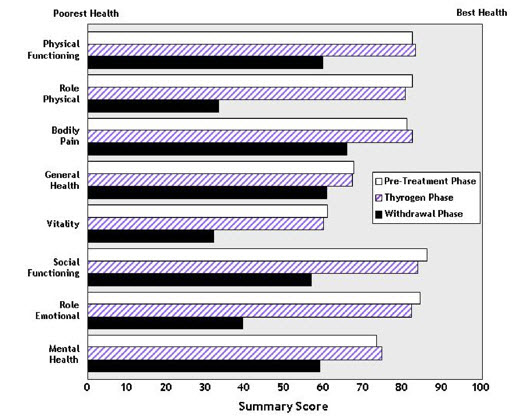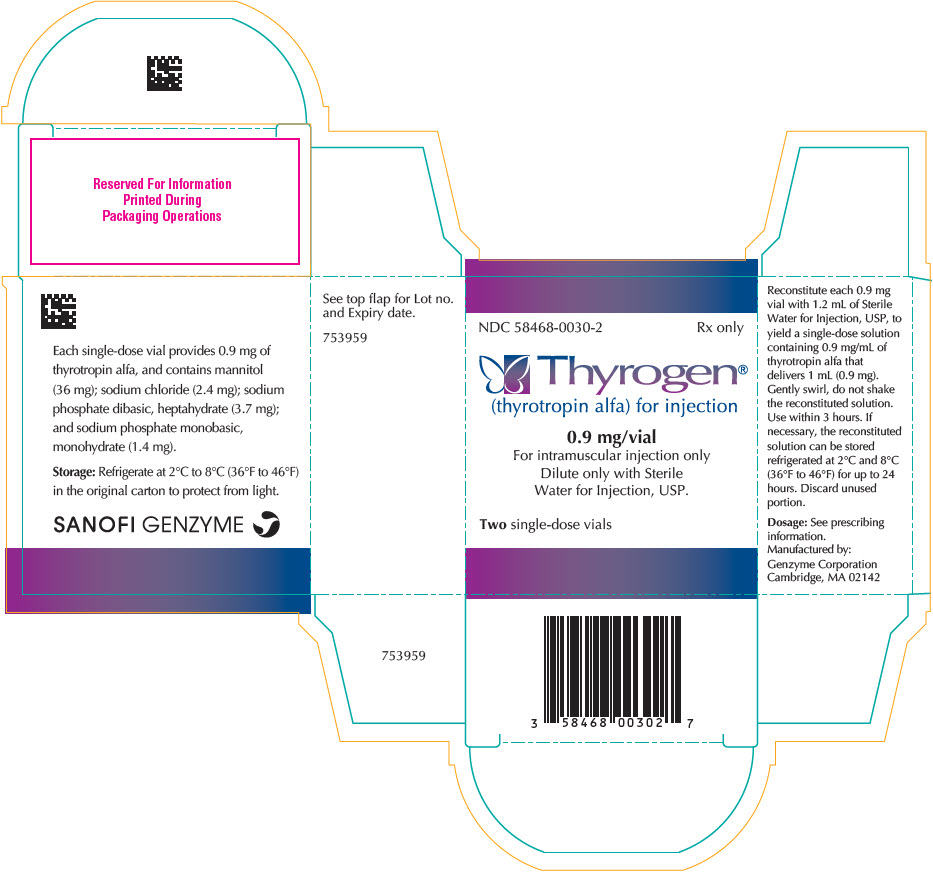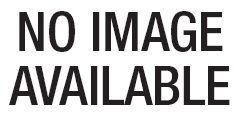 DRUG LABEL: Thyrogen
NDC: 58468-0030 | Form: INJECTION, POWDER, LYOPHILIZED, FOR SOLUTION
Manufacturer: Genzyme Corporation
Category: prescription | Type: HUMAN PRESCRIPTION DRUG LABEL
Date: 20230224

ACTIVE INGREDIENTS: THYROTROPIN ALFA 0.9 mg/1 mL
INACTIVE INGREDIENTS: MANNITOL 30 mg/1 mL; SODIUM PHOSPHATE 4.25 mg/1 mL; SODIUM CHLORIDE 2 mg/1 mL

HIGHLIGHTS OF PRESCRIBING INFORMATION

These highlights do not include all the information needed to use THYROGEN safely and effectively. See full prescribing information for THYROGEN.
THYROGEN® (thyrotropin alfa) for injection, for intramuscular use
Initial U.S. Approval: 1998

1 INDICATIONS AND USAGE

THYROGEN® is a thyroid stimulating hormone indicated for:

- Adjunctive Diagnostic Tool for Well-Differentiated Thyroid Cancer:
  Use as an adjunctive diagnostic tool for serum thyroglobulin (Tg) testing with or without radioiodine imaging in the follow-up of patients with well-differentiated thyroid cancer who have previously undergone thyroidectomy. (1.1)
  Limitations of Use:
  - THYROGEN-stimulated Tg levels are generally lower than, and do not correlate with Tg levels after thyroid hormone withdrawal.
  - Even when THYROGEN-Tg testing is performed in combination with radioiodine imaging, there remains a risk of missing a diagnosis of thyroid cancer or underestimating the extent of the disease.
  - Anti-Tg Antibodies may confound the Tg assay and render Tg levels uninterpretable.
- Adjunct for Thyroid Remnant Ablation in Well-Differentiated Thyroid Cancer: Use as an adjunctive treatment for radioiodine ablation of thyroid tissue remnants in patients who have undergone a near-total or total thyroidectomy for well-differentiated thyroid cancer and who do not have evidence of distant metastatic thyroid cancer. (1.2)
  Limitations of Use:
  - The effect of THYROGEN on thyroid cancer recurrence greater than 5 years post-remnant ablation has not been evaluated.

2 DOSAGE AND ADMINISTRATION

- THYROGEN should be used by physicians knowledgeable in the management of patients with thyroid cancer. (2.1)
- A two-injection regimen is recommended: THYROGEN 0.9 mg is administered intramuscularly, followed by a second 0.9 mg intramuscular injection 24 hours later. (2.1)

3 DOSAGE FORMS AND STRENGTHS

For injection: 0.9 mg of thyrotropin alfa as a lyophilized powder in a single-dose vial. (3)

4 CONTRAINDICATIONS

- If THYROGEN is administered with radioiodine, the contraindications to radioiodine also apply to this combination regimen. (4)

5 WARNINGS AND PRECAUTIONS

- THYROGEN-induced hyperthyroidism: Hospitalization for administration of THYROGEN and postadministrative observation should be considered for patients at risk. (5.1)
- Stroke: Stroke in female patients as well as other neurologic events in patients with central nervous system metastases. (5.2, 5.3)
- Sudden rapid tumor enlargement: Sudden, rapid and painful enlargement in distant metastatic thyroid cancer. (5.3)
- Risks associated with radioiodine (RAI) combination treatment: If THYROGEN is administered with RAI, the warnings and precautions for RAI also apply to this combination regimen. (5.4)

6 ADVERSE REACTIONS

The most common adverse reactions (>5%) reported in clinical trials were nausea and headache. (6.1)

To report SUSPECTED ADVERSE REACTIONS, contact Genzyme Corporation at 800-745-4447 or FDA at 1-800-FDA-1088 or www.fda.gov/medwatch.

8 USE IN SPECIFIC POPULATIONS

- Pregnancy: Concomitant use of THYROGEN and radioiodine (RAI) is contraindicated in pregnancy. (4, 8.1)
- Lactation: Concomitant use of THYROGEN and therapeutic RAI is contraindicated in lactating women. (4, 8.2)
- Renal Impairment: Elimination of THYROGEN is significantly slower in dialysis-dependent end-stage renal disease patients, resulting in prolonged elevation of TSH levels. (8.6)

FULL PRESCRIBING INFORMATION

1 INDICATIONS AND USAGE

1.1 Adjunctive Diagnostic Tool for Well-Differentiated Thyroid Cancer

THYROGEN® is indicated for use as an adjunctive diagnostic tool for serum thyroglobulin (Tg) testing with or without radioiodine imaging in the follow-up of patients with well-differentiated thyroid cancer who have previously undergone thyroidectomy.

Limitations of Use:

- THYROGEN-stimulated Tg levels are generally lower than, and do not correlate with, Tg levels after thyroid hormone withdrawal [see Clinical Studies (14.1)].
- Even when THYROGEN-stimulated Tg testing is performed in combination with radioiodine imaging, there remains a risk of missing a diagnosis of thyroid cancer or of underestimating the extent of disease.
- Anti-Tg antibodies may confound the Tg assay and render Tg levels uninterpretable [see Clinical Studies (14.1)]. Therefore, in such cases, even with a negative or low-stage THYROGEN radioiodine scan, consideration should be given to further evaluating patients.

1.2 Adjunct for Thyroid Remnant Ablation in Well-Differentiated Thyroid Cancer

THYROGEN is indicated for use as an adjunctive treatment for radioiodine ablation of thyroid tissue remnants in patients who have undergone a near-total or total thyroidectomy for well-differentiated thyroid cancer and who do not have evidence of distant metastatic thyroid cancer.

Limitations of Use:

- The effect of THYROGEN on thyroid cancer recurrence greater than five years post-remnant ablation has not been evaluated [see Clinical Studies (14.2)].

2 DOSAGE AND ADMINISTRATION

2.1 Recommended Dosage

THYROGEN should be used by physicians knowledgeable in the management of patients with thyroid cancer.

THYROGEN is indicated as a two-injection regimen. The recommended dosage of THYROGEN is a 0.9 mg intramuscular injection to the buttock followed by a second 0.9 mg intramuscular injection to the buttock 24 hours later.

THYROGEN should be administered intramuscularly only. THYROGEN should not be administered intravenously.

Pretreatment with glucocorticoids should be considered for patients in whom tumor expansion may compromise vital anatomic structures [see Warnings and Precautions (5.3)].

Routine measurement of serum TSH levels is not recommended after THYROGEN use.

2.2 Reconstitution, Preparation, and Administration of THYROGEN

The supplied lyophilized powder must be reconstituted with Sterile Water for Injection, USP. THYROGEN should be prepared, and administered in the following manner:

- Reconstitute each 0.9 mg vial of THYROGEN with 1.2 mL of Sterile Water for Injection, USP to yield a single-dose solution containing 0.9 mg/mL of thyrotropin alfa that delivers 1 mL (0.9 mg).
- Gently swirl the contents of the vial until all the material is dissolved. Do not shake the solution.
- Visually inspect the reconstituted solution for particulate matter and discoloration prior to administration. The reconstituted THYROGEN solution should be clear and colorless. Do not use if the solution has particulate matter or is cloudy or discolored.
- Withdraw 1 mL of the reconstituted THYROGEN solution (0.9 mg of thyrotropin alfa) and inject intramuscularly in the buttocks. Discard any unused portions.
- The reconstituted THYROGEN solution must be injected within 3 hours unless refrigerated.
- If necessary, the reconstituted solution can be stored refrigerated at a temperature between 2°C and 8°C (36°F to 46°F) for up to 24 hours, while avoiding microbial contamination.
- Do not mix with other substances.

2.3 Timing of Serum Thyroglobulin Testing Following THYROGEN Administration

For serum thyroglobulin testing, the serum sample should be obtained 72 hours after the final injection of THYROGEN [see Clinical Studies (14.1)].

2.4 Timing for Remnant Ablation and Diagnostic Scanning Following THYROGEN Administration

Oral radioiodine should be given 24 hours after the second injection of THYROGEN in both remnant ablation and diagnostic scanning. The activity of ^131I is carefully selected at the discretion of the nuclear medicine physician.

Diagnostic scanning should be performed 48 hours after the radioiodine administration.

3 DOSAGE FORMS AND STRENGTHS

For injection: 0.9 mg white to off-white lyophilized powder in a single-dose vial

4 CONTRAINDICATIONS

If THYROGEN is administered with radioiodine, the contraindications to radioiodine also apply to this combination regimen. Refer to the radioiodine prescribing information for a list of contraindications for radioiodine.

5 WARNINGS AND PRECAUTIONS

5.1 THYROGEN-Induced Hyperthyroidism

When given to patients who have substantial thyroid tissue still in situ or functional thyroid cancer metastases, THYROGEN is known to cause a transient (over 7 to 14 days) but significant rise in serum thyroid hormone concentration. There have been reports of death in non-thyroidectomized patients and in patients with distant metastatic thyroid cancer in which events leading to death occurred within 24 hours after administration of THYROGEN. Patients with residual thyroid tissue at risk for THYROGEN-induced hyperthyroidism include the elderly and those with a known history of heart disease. Hospitalization for administration of THYROGEN and postadministration observation in patients at risk should be considered.

5.2 Stroke

There are postmarketing reports of radiologically-confirmed stroke and neurological findings suggestive of stroke unconfirmed radiologically (e.g., unilateral weakness) occurring within 72 hours (range 20 minutes to three days) of THYROGEN administration in patients without known central nervous system metastases. The majority of such patients were young women taking oral contraceptives at the time of their event or had other risk factors for stroke, such as smoking or a history of migraine headaches. The relationship between THYROGEN administration and stroke is unknown. Patients should be well-hydrated prior to treatment with THYROGEN.

5.3 Sudden Rapid Tumor Enlargement

Sudden, rapid and painful enlargement of residual thyroid tissue or distant metastases can occur following treatment with THYROGEN. This may lead to acute symptoms, which depend on the anatomical location of the tissue. Such symptoms include acute hemiplegia, hemiparesis, and loss of vision one to three days after THYROGEN administration. Laryngeal edema, pain at the site of distant metastasis, and respiratory distress requiring tracheotomy have also been reported after THYROGEN administration.

Pretreatment with glucocorticoids should be considered for patients in whom tumor expansion may compromise vital anatomic structures.

5.4 Risks Associated with Radioiodine Treatment

If THYROGEN is administered with radioiodine (RAI), the warnings and precautions for RAI, apply to this combination regimen. Refer to the RAI prescribing information for a full list of the warnings and precautions for RAI.

6 ADVERSE REACTIONS

6.1 Clinical Trials Experience

Because clinical trials are conducted under widely varying conditions, adverse reaction rates observed in the clinical trials of a drug cannot be directly compared to rates in the clinical trials of another drug and may not reflect the rates observed in practice.

The data described below reflect exposure to THYROGEN in 481 thyroid cancer patients who participated in a total of 6 clinical trials of THYROGEN: 4 trials for diagnostic use and 2 trials for ablation. In clinical trials, patients had undergone near-total thyroidectomy and had a mean age of 46.1 years. Thyroid cancer diagnosis was as follows: papillary (69.2%), follicular (12.9%), Hurthle cell (2.3%) and papillary/follicular (15.6%). Most patients received 2 intramuscular injections of 0.9 mg of THYROGEN injection gin 24 hours apart [see Clinical Studies (14.1, 14.2)].

The safety profile of patients who have undergone thyroidectomy and received THYROGEN as adjunctive treatment for radioiodine ablation of thyroid tissue remnants for well-differentiated thyroid cancer did not differ from that of patients who received THYROGEN for diagnostic purposes.

Reactions reported in ≥1% of patients in the combined trials are summarized in Table 1. In some studies, an individual patient may have participated in both THYROGEN and thyroid hormone withdrawal [see Clinical Studies (14.1, 14.2)].

Table 1: Summary of Adverse Reactions by THYROGEN and Thyroid Hormone Withdrawal in Pooled Clinical Trials (≥1% of Patients in any Phase)
 | THYROGEN | Thyroid Hormone Withdrawal
 | (N=481) | (N=418)
Preferred Term | n (%) | n (%)
Nausea | 53 (11) | 2 (<1)
Headache | 29 (6) | 0
Fatigue | 11 (2) | 2 (<1)
Vomiting | 11 (2) | 0
Dizziness | 9 (2) | 0 (0.0)
Asthenia | 5 (1) | 1 (<1)

6.2 Postmarketing Experience

The following adverse reactions have been identified during postapproval use of THYROGEN. Because these reactions are reported voluntarily from a population of uncertain size, it is not always possible to reliably estimate their frequency or establish a causal relationship to drug exposure.

- Transient (<48 hours) influenza-like symptoms, including fever (>100°F/38°C), chills/shivering, myalgia/arthralgia, fatigue/asthenia/malaise, headache, and chills.
- Hypersensitivity including urticaria, rash, pruritus, flushing, and respiratory signs and symptoms.
- Injection site reactions, including pain, erythema, bruising, and pruritus.

8 USE IN SPECIFIC POPULATIONS

8.1 Pregnancy

Risk Summary

THYROGEN may be used in combination with radioiodine (RAI). If THYROGEN is administered with RAI, the combination regimen is contraindicated in pregnant women because fetal exposure to RAI can lead to neonatal hypothyroidism, which in some cases is severe and irreversible. Refer to the RAI prescribing information for more information on use during pregnancy.

Available data from case reports and postmarketing experience with THYROGEN use in pregnant women are insufficient to evaluate for a drug-associated risk of major birth defects, miscarriage, or adverse maternal or fetal outcomes. Animal reproduction studies have not been conducted with THYROGEN.

The estimated background risk of major birth defects and miscarriage for the indicated population is unknown. In the U.S. general population, the estimated background risk of major birth defects and miscarriage in clinically recognized pregnancies is 2% to 4% and 15% to 20%, respectively.

8.2 Lactation

Risk Summary

The concomitant use of THYROGEN and therapeutic radioiodine (RAI) is contraindicated in lactating women because RAI concentrates in the breast tissue and increases the risk of radiation breast toxicity (refer to the therapeutic RAI Prescribing Information).

If THYROGEN is administered with RAI for diagnostic use, discontinue breastfeeding after RAI administration because of the potential for serious adverse reactions from RAI in the breastfed infant (refer to the diagnostic RAI Prescribing Information).

If THYROGEN is not administered with RAI, the developmental and health benefits of breastfeeding should be considered along with the mother's clinical need for THYROGEN and any potential adverse effects on the breastfed child from THYROGEN or from the underlying maternal condition.

There are no available data on the presence of thyrotropin alfa in human milk, the effects on the breastfed infant, or the effects on milk production.

8.3 Females and Males of Reproductive Potential

THYROGEN may be used in combination with radioiodine (RAI). If THYROGEN is administered with RAI, the information for RAI regarding pregnancy testing, contraception, and infertility also applies to the combination regimen. Refer to the RAI prescribing information for additional information.

8.4 Pediatric Use

Safety and effectiveness in pediatric patients have not been established.

8.5 Geriatric Use

In pooled clinical studies of THYROGEN, 60 patients (12%) were >65 years, and 421 (88%) were ≤65 years of age. Results from controlled trials do not indicate a difference in the safety and efficacy of THYROGEN between adult patients less than 65 years and those over 65 years of age [see Warnings and Precautions (5.1)].

8.6 Renal Impairment

Elimination of THYROGEN is significantly slower in dialysis-dependent end-stage renal disease (ESRD) patients, resulting in prolonged elevation of TSH levels.

10 OVERDOSAGE

In clinical trials of THYROGEN, three patients experienced symptoms after receiving THYROGEN doses higher than those recommended. Two patients had nausea after a 2.7 mg IM dose (3 times the recommended dose), and in one of these patients, the event was accompanied by weakness, dizziness and headache. Another patient experienced nausea, vomiting and hot flashes after a 3.6 mg IM dose (4 times the recommended dose). There is no specific therapy for THYROGEN overdose. Supportive care is recommended.

11 DESCRIPTION

Thyrotropin alfa, a recombinant human thyroid stimulating hormone, is a heterodimeric glycoprotein comprised of two non-covalently linked subunits, an alpha subunit of 92 amino acid residues containing two N-linked glycosylation sites and a beta subunit of 118 residues containing one N-linked glycosylation site. The amino acid sequence of thyrotropin alfa is identical to that of human pituitary TSH. Thyrotropin alfa is synthesized in a genetically modified Chinese hamster ovary cell line.

Both thyrotropin alfa and naturally occurring human pituitary TSH are synthesized as a mixture of glycosylation variants. Unlike pituitary TSH, which is secreted as a mixture of sialylated and sulfated forms, thyrotropin alfa is sialylated but not sulfated. The biological activity of thyrotropin alfa is determined by a cell-based bioassay. In this assay, cells expressing a functional TSH receptor and a cAMP-responsive element coupled to a heterologous reporter gene, luciferase, enable the measurement of thyrotropin alfa activity by measuring the luciferase response. The specific activity of thyrotropin alfa is determined relative to an internal Genzyme reference standard that was calibrated against the World Health Organization (WHO) human TSH reference standard.

THYROGEN (thyrotropin alfa) for injection is a sterile, white to off-white lyophilized powder in a single-dose vial for intramuscular use after reconstitution.

Each single-dose vial provides 0.9 mg of thyrotropin alfa, and contains mannitol (36 mg); sodium chloride (2.4 mg);sodium phosphate dibasic, heptahydrate (3.7 mg); and sodium phosphate monobasic, monohydrate (1.4 mg). After reconstitution with 1.2 mL of Sterile Water for Injection, USP, the concentration is 0.9 mg/mL with a deliverable volume of 1 mL (0.9 mg) and a pH of approximately 6.5 to 7.5.

12 CLINICAL PHARMACOLOGY

12.1 Mechanism of Action

Thyrotropin (TSH) is a pituitary hormone that stimulates the thyroid gland to produce thyroid hormone. Binding of thyrotropin alfa to TSH receptors on normal thyroid epithelial cells or on well-differentiated thyroid cancer tissue stimulates iodine uptake and organification, and synthesis and secretion of thyroglobulin (Tg), triiodothyronine (T3) and thyroxine (T4).

The effect of thyroid stimulating hormone activation of thyroid cells is to increase uptake of radioiodine to allow scan detection or radioiodine killing of thyroid cells. TSH activation also leads to the release of thyroglobulin by thyroid cells. Thyroglobulin functions as a tumor marker which is detected in blood specimens.

12.3 Pharmacokinetics

The pharmacokinetics of THYROGEN was studied in 16 patients with well-differentiated thyroid cancer given a single 0.9 mg IM dose. Mean peak serum TSH concentrations of 116±38 mU/L were reached between 3 and 24 hours after injection (median of 10 hours). The mean apparent elimination half-life was 25±10 hours. The organ(s) of TSH clearance in man have not been identified, but studies of pituitary-derived TSH suggest the involvement of the liver and kidneys.

13 NONCLINICAL TOXICOLOGY

13.1 Carcinogenesis, Mutagenesis, Impairment of Fertility

Long-term toxicity studies in animals have not been performed with THYROGEN to evaluate the carcinogenic potential of the drug. THYROGEN was not mutagenic in the bacterial reverse mutation assay. Studies have not been performed with THYROGEN to evaluate the effects on fertility.

14 CLINICAL STUDIES

14.1 Clinical Trials of THYROGEN as an Adjunctive Diagnostic Tool for Well-Differentiated Thyroid Cancer

Two prospective, randomized phase 3 clinical trials were conducted in patients with well-differentiated thyroid cancer to compare ^131I whole body scans obtained after THYROGEN injection to ^131I whole body scans after thyroid hormone withdrawal. A cross-over, non-blinded design was used in both trials. Oral radioiodine was given 24 hours after the second injection of THYROGEN, and scanning was done 48 hours after the radioiodine administration. Each patient was scanned first following THYROGEN and then scanned after thyroid hormone withdrawal. In both studies, the primary endpoint was the rate of concordant scans (scan findings in agreement in a given patient using each preparation method).

Study 1 (n=127) compared the diagnostic scanning following a THYROGEN regimen of 0.9 mg IM daily on two consecutive days to thyroid hormone withdrawal. In addition to body scans, Study 2 (n=229) also compared thyroglobulin (Tg) levels obtained after THYROGEN to those at baseline and to those after thyroid hormone withdrawal. All Tg testing was performed in a central laboratory using a radioimmunoassay (RIA) with a functional sensitivity of 2.5 ng/mL. Patients who were included in the Tg analysis were those who had undergone total or near-total thyroidectomy with or without ^131I ablation, had <1% uptake in the thyroid bed on a scan after thyroid hormone withdrawal, and did not have detectable anti-Tg antibodies. The maximum THYROGEN Tg value was obtained 72 hours after the final THYROGEN injection, and this value was used in the analysis.

Diagnostic Radioiodine Whole Body Scan Results

Study 1 enrolled 127 patients, 71% were female and 29% male, and mean age was 44 years. The study included the following forms of differentiated thyroid cancer: papillary cancer (88%), follicular cancer (9%), and Hurthle cell (2%). Study results are displayed in Table 2.

In Study 2, patients with differentiated thyroid cancer who had been thyroidectomized (n=229) were randomized into one of two THYROGEN treatment regimens: THYROGEN 0.9 mg IM daily on two consecutive days (n=117), and THYROGEN 0.9 mg IM daily on days 1, 4 and 7 (n=112). Each patient was scanned first using THYROGEN, then scanned using thyroid hormone withdrawal. The group receiving the THYROGEN 0.9 mg IM × 2 regimen was 63% female/27% male, had a mean age of 44 years, and generally had low-stage papillary or follicular cancer (AJCC/TNM Stage I 61%, Stage II 19%, Stage III 14%, Stage IV 5%). The group receiving the THYROGEN 0.9 mg IM × 3 regimen was 66% female/34% male, had a mean age of 50 years, and generally had low-stage papillary or follicular cancer (AJCC/TNM Stage I 50%, Stage II 20%, Stage III 20%, Stage IV 9%). The amount of radioiodine used for scanning was 4 mCi ± 10%, and scanning times were lengthened in some patients to capture adequate images (30 minute scans, or 140,000 counts). Scan pairs were assessed by blinded readers. Study results are presented in Table 2.

Table 2: Concordance of Positive Thyroid Scans Following THYROGEN Treatment with Scans Following Thyroid Hormone Withdrawal
 | Number of scan pairs by disease category | Concordance of scan pairs between THYROGEN scan and thyroid hormone withdrawal scan
Study 1 (0.9 mg IM qd × 2)
Positive for remnant or cancer in thyroid bed | 48 | 81%
Positive for metastatic disease | 15 | 73%
Total positive withdrawal scans [Across both studies uptake was detected on the THYROGEN scan but not observed on the scan after thyroid hormone withdrawal in 5 patients with remnant or cancer in the thyroid bed.] , [In the two clinical studies radioiodine scan results using thyroid hormone withdrawal were taken as the true clinical status of each patient and as the comparator for THYROGEN scans. Thyroid hormone withdrawal trace-positive scans were scored conservatively as positive with no allowance for false positives.] | 63 | 79%
Study 2 (0.9 mg IM qd × 2)
Positive for remnant or cancer in thyroid bed | 35 | 86%
Positive for metastatic Disease | 9 | 67%
Total positive withdrawal scans, | 44 | 82%

Across the two clinical studies, and scoring all false positives in favor of thyroid hormone withdrawal, the majority of positive scans using THYROGEN and thyroid hormone withdrawal were concordant. The THYROGEN scan failed to detect remnant and/or cancer localized to the thyroid bed in 17% (14/83) of patients in whom it was detected by a scan after thyroid hormone withdrawal. In addition, the THYROGEN scan failed to detect metastatic disease in 29% (7/24) of patients in whom it was detected by a scan after thyroid hormone withdrawal.

Thyroglobulin (Tg) Results

THYROGEN Tg testing alone and in combination with diagnostic whole body scanning: comparison with results after thyroid hormone withdrawal

In anti-Tg antibody negative patients with a thyroid remnant or cancer (as defined by a withdrawal Tg ≥2.5 ng/mL or a positive scan [after thyroid hormone withdrawal or after radioiodine therapy]), the THYROGEN Tg was positive (≥2.5 ng/mL) in 69% (40/58) of patients after 2 doses of THYROGEN.

In these same patients, adding the whole body scan increased the detection rate of thyroid remnant or cancer to 84% (49/58) of patients after 2 doses of THYROGEN.

Among patients with metastatic disease confirmed by a post-treatment scan or by lymph node biopsy (35 patients), THYROGEN Tg was positive (≥2.5 ng/mL) in all 35 patients, while Tg on thyroid hormone suppressive therapy was positive (≥2.5 ng/mL) in 79% of these patients.

As with thyroid hormone withdrawal, the intra-patient reproducibility of THYROGEN testing with regard to both Tg stimulation and radioiodine imaging has not been studied.

Hypothyroid Signs and Symptoms

THYROGEN administration was not associated with the signs and symptoms of hypothyroidism that accompanied thyroid hormone withdrawal as measured by the Billewicz scale. Statistically significant worsening in all signs and symptoms were observed during the hypothyroid phase (p<0.01) (Figure 1).

Figure 1: Hypothyroid Symptom Assessment Billewicz Scale Diagnostic Indication 0.9 mg THYROGEN q 24 hours × 2 doses vs Thyroid Hormone Withdrawal Phase

14.2 Clinical Trials of THYROGEN as an Adjunct for Thyroid Remnant Ablation in Well-Differentiated Thyroid Cancer

A randomized, prospective clinical trial compared the rates of thyroid remnant ablation achieved after preparation of patients with thyroid hormone withdrawal or THYROGEN. Patients (n=63) with low-risk, well-differentiated thyroid cancer who underwent near-total thyroidectomy were made euthyroid after surgery by receiving thyroid hormone replacement and were subsequently randomized to a thyroid hormone withdrawal or THYROGEN. Patients in the THYROGEN group received THYROGEN 0.9 mg IM daily on 2 consecutive days and radioiodine 24 hours after the second dose of THYROGEN. Patients in the thyroid hormone withdrawal group had the thyroid replacement withheld until they became hypothyroid. Patients in both groups received 100 mCi ^131I ± 10% with the intent to ablate any thyroid remnant tissue. The primary endpoint of the study was the rate of successful ablation, and was assessed 8 months later by a THYROGEN-stimulated radioiodine scan. Patients were considered successfully ablated if there was no visible thyroid bed uptake on the scan, or if visible, uptake was less than 0.1%. Table 3 summarizes the results of this evaluation.

Table 3: Remnant Ablation in Clinical Trial of Patients with Well-Differentiated Thyroid Cancer
Group [60 per protocol patients with interpretable scan data. 95% CI for difference in ablation rates THYROGEN minus Thyroid Hormone Withdrawal, = 7% to 27%.] | Mean Age (Yr) | Gender (F:M) | Cancer Type (Pap:Fol) | Ablation Criterion (Measure at 8 Months)
 |  |  |  | Thyroid Bed Activity <0.1% | No Visible Thyroid Bed Activity [Interpretation by 2 of 3 reviewers. 95% CI for difference in ablation rates, THYROGEN minus Thyroid Hormone Withdrawal, = -31% to 9%.]
Thyroid Hormone Withdrawal (N=28) | 43 | 24:6 | 29:1 | 28/28 (100%) | 24/28 (86%)
THYROGEN (N=32) | 44 | 26:7 | 30:3 | 32/32 (100%) | 24/32 (75%)
Abbreviations: fol = follicular, pap = papillary

The mean radiation dose to blood was 0.266 ± 0.061 mGy/MBq in the THYROGEN group and 0.395 ± 0.135 mGy/MBq in the thyroid hormone withdrawal group. Radioiodine residence time in remnant tissue was 0.9 ± 1.3 hours in the THYROGEN group and 1.4 ± 1.5 hours in the thyroid hormone withdrawal group. It is not known whether this difference in radiation exposure would convey a clinical benefit.

Patients who completed were followed up for a median duration of 3.7 years (range 3.4 to 4.4 years) following radioiodine ablation. Tg testing was also performed. The main objective of the follow-up study was to evaluate the status of thyroid remnant ablation by using THYROGEN-stimulated neck imaging. Of the fifty-one patients enrolled, forty-eight patients received THYROGEN for remnant neck/whole body imaging and/or thyroglobulin testing. Only 43 patients had imaging. Patients were still considered to be successfully ablated if there was no visible thyroid bed uptake on the scan, or if visible, uptake was less than 0.1%. All patients from both original treatment groups who had scanning were found to still be ablated. Of 37 patients who were Tg-antibody negative, 16/17 (94%) of patients in the former thyroid hormone withdrawal group and 19/20 (95%) of patients in the former THYROGEN group maintained successful ablation measured as stimulated serum Tg levels of <2 ng/mL.

No patient had a definitive cancer recurrence during the 3.7 years of follow-up. Overall, 48/51 patients (94%) had no evidence of cancer recurrence, 1 patient had possible cancer recurrence (although it was not clear whether this patient had a true recurrence or persistent tumor from the regional disease noted at the start of the initial study), and 2 patients could not be assessed.

Two large prospective multicenter randomized studies compared THYROGEN to thyroid hormone withdrawal using two different doses of radioactive iodine in patients with differentiated thyroid cancer who had been thyroidectomized. In both studies, patients were randomized to 1 of 4 treatment groups: THYROGEN + 30 mCi ^131I, THYROGEN + 100 mCi ^131I, thyroid hormone withdrawal + 30 mCi ^131I, or thyroid hormone withdrawal + 100 mCi ^131I. Patients were assessed for efficacy (ablation success rates) at approximately 8 months.

The first study (Study A) randomized 438 patients (tumor stages T1–T3, Nx, N0 and N1, M0). Ablation success was defined as radioiodine uptake of <0.1% in the thyroid bed and stimulated thyroglobulin levels of <2.0 ng/mL. Results are summarized below (Table 4).

Table 4: Remnant Ablation Rates in Study A
 | THYROGEN | Thyroid Hormone Withdrawal | Total
Low-dose radioiodine | 91/108 (84.3%) | 91/106 (85.8%) | 182/214 (85.0%)
High-dose Radioiodine | 92/102 (90.2%) | 92/105 (87.6%) | 184/207 (88.9%)
Total | 183/210 (87.1%) | 183/211 (86.7%) | 366/421 (86.9%)
95% CI of difference in ablation rate (low dose minus high dose): -10.2% to 2.6%
95% CI of difference in ablation rate (THYROGEN - Thyroid Hormone Withdrawal): -6.0% to 6.8%

For Study A, 434 (99%) of the original 438 patients were followed up for disease recurrence. The median follow-up was 6.5 years (0.03 to 10.6 years).

The second study (Study B) randomized 752 patients with low-risk thyroid cancer (tumor stages pT1 <1 cm and N1 or Nx, pT1 >1–2 cm and any N stage, or pT2 N0, all patients M0). Ablation success was defined by neck ultrasound and stimulated thyroglobulin of ≤1.0 ng/mL. Results are summarized below (Table 5).

Table 5: Remnant Ablation Rates in Study B
 | THYROGEN | Thyroid Hormone Withdrawal | Total
Low-dose radioiodine | 160/177 (90.4%) | 156/170 (91.8%) | 316/347 (91.1%)
High-dose Radioiodine | 159/171 (93.0%) | 156/166 (94.0%) | 315/337 (93.5%)
Total | 319/348 (91.6%) | 312/336 (92.9%) | 631/684 (92.3%)
95% CI of difference in ablation rate (low dose minus high dose): -5.8% to 0.9%
95% CI of difference in ablation rate (THYROGEN minus Thyroid Hormone Withdrawal): -4.5% to 2.2%

For Study B, 726 (97%) of the original 752 patients were followed up for disease recurrence. The median follow-up was 5.4 years (0.5 to 9.2 years).

Five-year follow-up data of THYROGEN for remnant ablation with two different RAI doses in Study A and Study B observed similar rates of thyroid cancer recurrence as thyroid hormone withdrawal.

14.3 Quality of Life

Quality of Life (QOL) was measured during both the diagnostic study [see Clinical Studies (14.1)] and the ablation of thyroid remnant study [see Clinical Studies (14.2)] using the SF-36 Health Survey, a standardized, patient-administered instrument assessing QOL across eight domains measuring both physical and mental functioning. In the diagnostic study and in the remnant ablation study, following THYROGEN administration, little change from baseline was observed in any of the eight QOL domains of the SF-36. Following thyroid hormone withdrawal in the diagnostic study, statistically significant negative changes were noted in all eight QOL domains of the SF-36. The difference between treatment groups was statistically significant (p<0.0001) for all eight QOL domains, favoring THYROGEN over thyroid hormone withdrawal (Figure 2). In the remnant ablation study, following thyroid hormone withdrawal, statistically significant negative changes were noted in five of the eight QOL domains (physical functioning, role physical, vitality, social functioning and mental health).

Figure 2: SF-36 Health Survey Results Quality of Life Domains Diagnostic Indication

16 HOW SUPPLIED/STORAGE AND HANDLING

THYROGEN (thyrotropin alfa) for injection is as a sterile white to off-white lyophilized powder in a single-dose vial. Each carton (NDC 58468-0030-2) contains two 0.9 mg single-dose vials of THYROGEN (NDC 58468-0030-1).

STORAGE AND HANDLING

Store THYROGEN refrigerated at 2°C to 8°C (36°F to 46°F) in the original carton to protect from light.

17 PATIENT COUNSELING INFORMATION

Adverse Reactions

- Inform patients that the most common adverse events from clinical experience were nausea and headache.
- Advise patients to seek immediate medical attention should they experience severe symptoms.

Important Information

- Prior to THYROGEN administration, counsel patients to seek care immediately for any neurologic symptoms occurring after administration of the drug.
- Inform patients for whom THYROGEN induced hyperthyroidism could have serious consequences, hospitalization for administration of THYROGEN and postadministrative observation should be considered.

Dosing and Administration

- Patients should be instructed that THYROGEN is for intramuscular administration into the buttock only. THYROGEN should not be administered intravenously.
- Inform patients the treatment regimen is two doses of THYROGEN administered at a 24 hour interval.
- Encourage patients to remain hydrated prior to treatment with THYROGEN.

Schedule of Procedures

- Inform patients that if diagnostic scanning will be performed, radioiodine will be given 24 hours after the second injection of THYROGEN, and patients should return for the scan 48 hours after radioiodine administration.
- Inform patients that if serum Tg testing is performed, blood will be drawn 72 hours or later after the second injection of THYROGEN.
- Inform patients that if remnant ablation is performed radioiodine will be administered 24 hours after the second injection of THYROGEN.

Pregnancy and Lactation Risks Associated with Radioiodine Treatment

- When THYROGEN is administered in combination with radioiodine (RAI), refer to the RAI prescribing information for patient counseling information. Inform patients to notify their healthcare provider immediately in the event of a pregnancy [see Warnings and Precautions (5.4) and Use in Specific Populations (8.1, 8.3)].

Manufactured by:
Genzyme Corporation
Cambridge, MA 02141
A SANOFI COMPANY

THYROGEN is a registered trademark of Genzyme Corporation.

PRINCIPAL DISPLAY PANEL - 2 Vial Carton

NDC 58468-0030-2
Rx only

Thyrogen®
(thyrotropin alfa) for injection

0.9 mg/vial
For intramuscular injection only
Dilute only with Sterile
Water for Injection, USP.

Two single-dose vials

Package Label - Principal Display Panel – 4 vial Carton